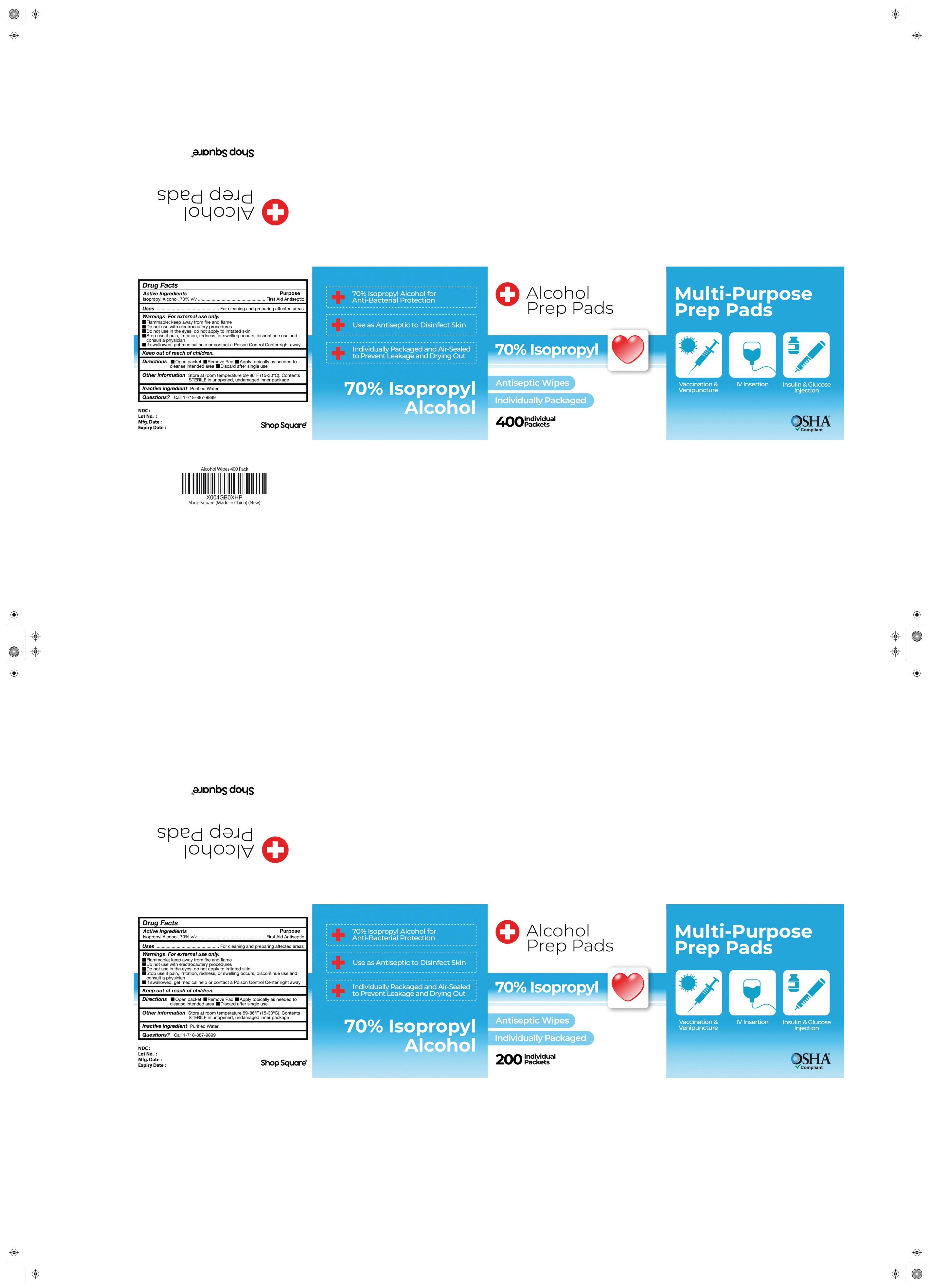 DRUG LABEL: ALCOHOL PREP AWABS
NDC: 85244-001 | Form: PATCH
Manufacturer: Henan Bingqing Yujie wipes Co., LTD
Category: otc | Type: HUMAN OTC DRUG LABEL
Date: 20250410

ACTIVE INGREDIENTS: ALCOHOL 70 g/100 1
INACTIVE INGREDIENTS: WATER

85244-001

Active Ingredient

Isopropyl Aicohol, 70% v/v

Purpose

Antiseptic

Use

External use

Warnings

Flammable.keep away from fire or flame

Do not use with electrocautery proceduresor in the eyes

Stop Use

Stop use if redness or irritationdevelops.discontinue use and consulta physician

Keep Out Of Reach Of Children

Directions

Open packet /Remove pad/ Apply topically as needed to cleanse intende area/ Discard after single use

Other information

Store at room temperature 59-86℉(15-30°C).ContentsSTERlLE in unopened, undamaged package

Inactive ingredients

Water

Questions

call-1-718-887-9899